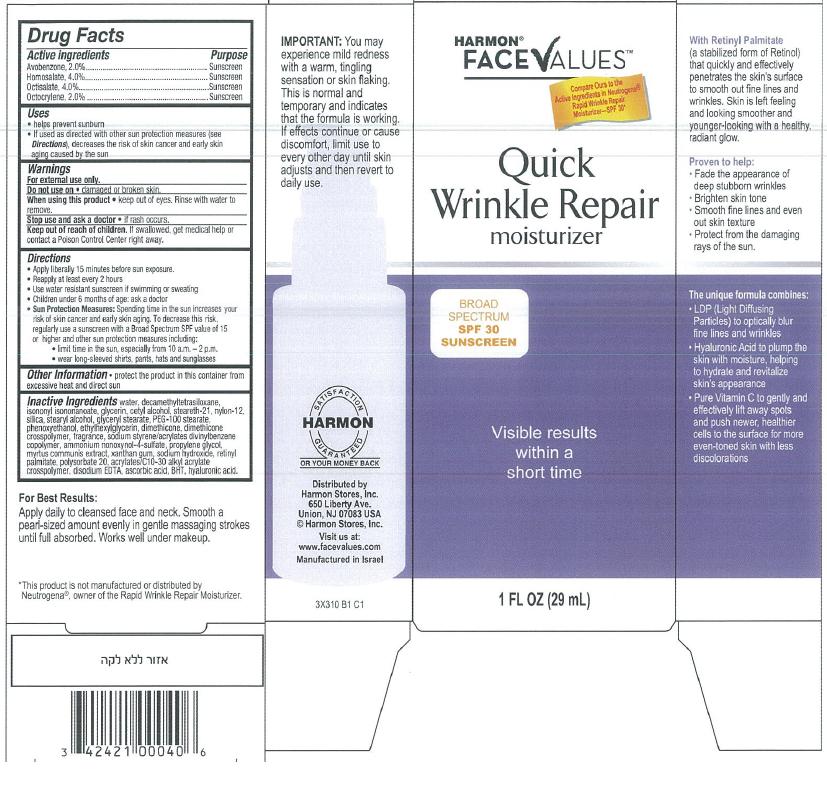 DRUG LABEL: Quick Wrinkle Repair Moisturizer Broad Spectrum SPF30
NDC: 63940-310 | Form: CREAM
Manufacturer: Harmon Stores Inc
Category: otc | Type: HUMAN OTC DRUG LABEL
Date: 20131112

ACTIVE INGREDIENTS: AVOBENZONE 2 g/100 mL; HOMOSALATE 4 g/100 mL; OCTISALATE 4 g/100 mL; OCTOCRYLENE 2 g/100 mL
INACTIVE INGREDIENTS: WATER; DECAMETHYLTETRASILOXANE; ISONONYL ISONONANOATE; GLYCERIN; CETYL ALCOHOL; STEARETH-21; NYLON-12; SILICON DIOXIDE; STEARYL ALCOHOL; GLYCERYL MONOSTEARATE; PEG-100 STEARATE; PHENOXYETHANOL; ETHYLHEXYLGLYCERIN; DIMETHICONE; DIMETHICONE/DIENE DIMETHICONE CROSSPOLYMER; AMMONIUM NONOXYNOL-4 SULFATE; PROPYLENE GLYCOL; MYRTUS COMMUNIS LEAF; XANTHAN GUM; SODIUM HYDROXIDE; VITAMIN A PALMITATE; POLYSORBATE 20; EDETATE DISODIUM; ASCORBIC ACID; BUTYLATED HYDROXYTOLUENE; HYALURONIC ACID; SODIUM POLYSTYRENE SULFONATE; CARBOMER INTERPOLYMER TYPE A (ALLYL SUCROSE CROSSLINKED)

Harmon® FaceValues™ Quick Wrinkle Repair Moisturizer

Active ingredient

Avobenzone 2.0%
Homosalate 4.0%
Octisalate 4.0%
Octocrylene 2.0%

Purpose

Sunscreen

Uses

- helps prevent sunburn
- If used as directed with other sun protection measures (see Directions), decreases the risk of skin cancer and early skin aging caused by the sun

Warnings

For external use only.

Do not use on

- damaged or broken skin.

When using this product

- keep out of eyes. Rinse with water to remove.

Stop use and ask a doctor

- if rash occurs.

Keep Out of Reach of Children.

If swallowed, get medical help or contact a Poison Control Center right away.

Directions

- Apply liberally 15 minutes before sun exposure.
- Reapply at least every 2 hours
- Use water resistant sunscreen if swimming or sweating
- Children under 6 months of age: ask a doctor
- Sun Protection Measures: Spending time in the sun increases your risk of skin cancer and early skin aging. To decrease this risk, regularly use a sunscreen with a Broad Spectrum SPF value of 15 or higher and other sun protection measures including:
  - limit time in the sun, especially from 10 a.m. - 2 p.m.
  - wear long-sleeved shirts, pants, hats and sunglasses

For Best Results:

Apply daily to cleansed face and neck. Smooth a pearl-sized amount evenly in gentle massaging strokes until full absorbed. Works well under makeup.

Other Information

- protect the product in this container from excessive heat and direct sun

Inactive ingredients

water, decamethyltetrasiloxane, isononyl isononanoate, glycerin, cetyl alcohol, steareth-21, nylon-12, silica, stearyl alcohol, glyceryl stearate, PEG-100 stearate, phenoxyethanol, ethylhexylglycerin, dimethicone, dimethicone crosspolymer, fragrance, sodium styrene/acrylates divinylbenzene copolymer, ammonium nonoxynol-4-sulfate, propylene glycol, myrtus communis extract, xanthan gum, sodium hydroxide, retinyl palmitate, polysorbate 20, acrylates/C10-30 alkyl acrylate crosspolymer, disodium EDTA, ascorbic acid, BHT, hyaluronic acid

Package/Label Principal Display Panel

Harmon® FaceValuesTM Quick Wrinkle Repair Moisturizer
Broad Spectrum SPF30 Sunscreen
Visible results within a short time

Compare Ours to the Active Ingredients in Neutrogena®
Rapid Wrinkle Repair Moisturizer - SPF 30*

1 Fl Oz (29 mL)

Distributed by

Harmon Stores, Inc.
650 Liberty Ave.
Union, NJ 07083 USA
©Harmon Stores, Inc.
Visit us at:
www.facevalues.com

Manufactured in Israel

3X310 B1 C1

*This product is not manufactured or distributed by Neutrogena®, owner of the Rapid Wrinkle Repair Moisturizer.

Label